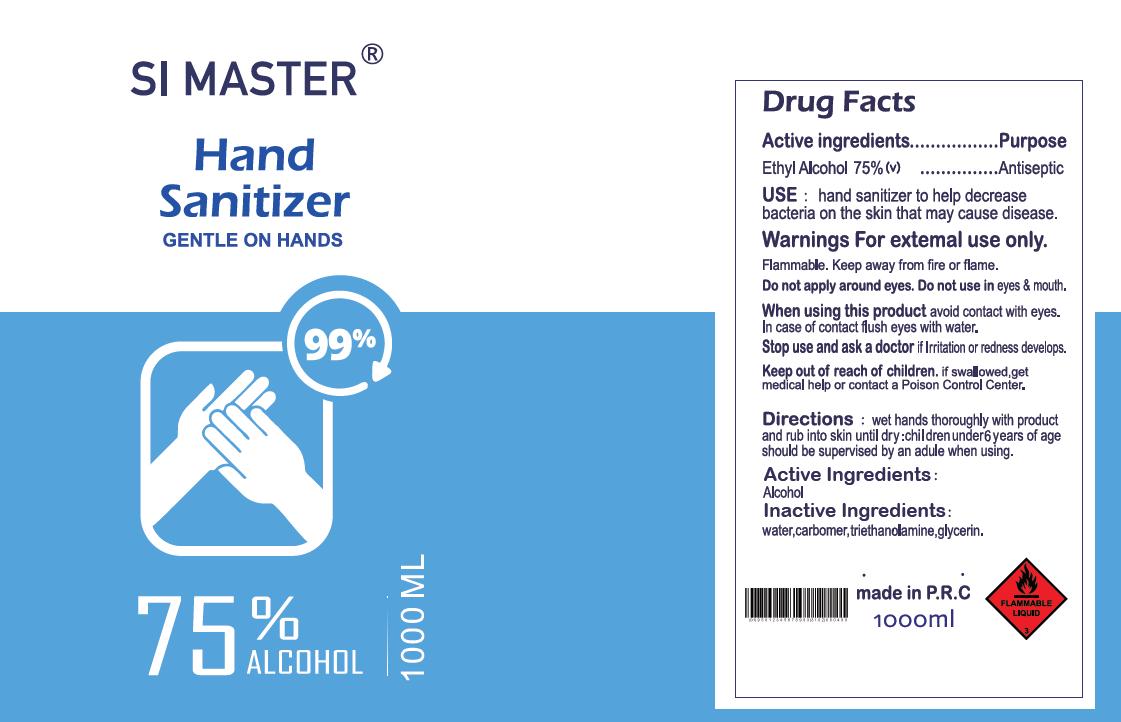 DRUG LABEL: SI MASTER Hand Sanitizer
NDC: 78852-000 | Form: GEL
Manufacturer: Ningbo Youcheng Trade Developing Co., Ltd.
Category: otc | Type: HUMAN OTC DRUG LABEL
Date: 20200615

ACTIVE INGREDIENTS: ALCOHOL 75 mL/100 mL
INACTIVE INGREDIENTS: WATER; CARBOMER HOMOPOLYMER, UNSPECIFIED TYPE; GLYCERIN; TROLAMINE

Active ingredients

Ethyl Alcohol 75%(v)

Purpose

Antiseptic

Use

hand sanitizer to help decrease bacteria on the skin that may cause disease.

Warnings

Warnings for external use only.

Flammable. Keep away from fire or flame.

DO NOT USE

Do not apply around eyes. Do not use in eyes & mouth.

When using this product avoid contact with eyes.

In case of contact flush eyes with water.

Stop use and ask a doctor if lrritation or redness develops.

Keep out of reach of children, if swallowed, get medical help or contact a Poison Control Center.

Inactive ingredients

water, carbomer, triethanolamine, glycerin.